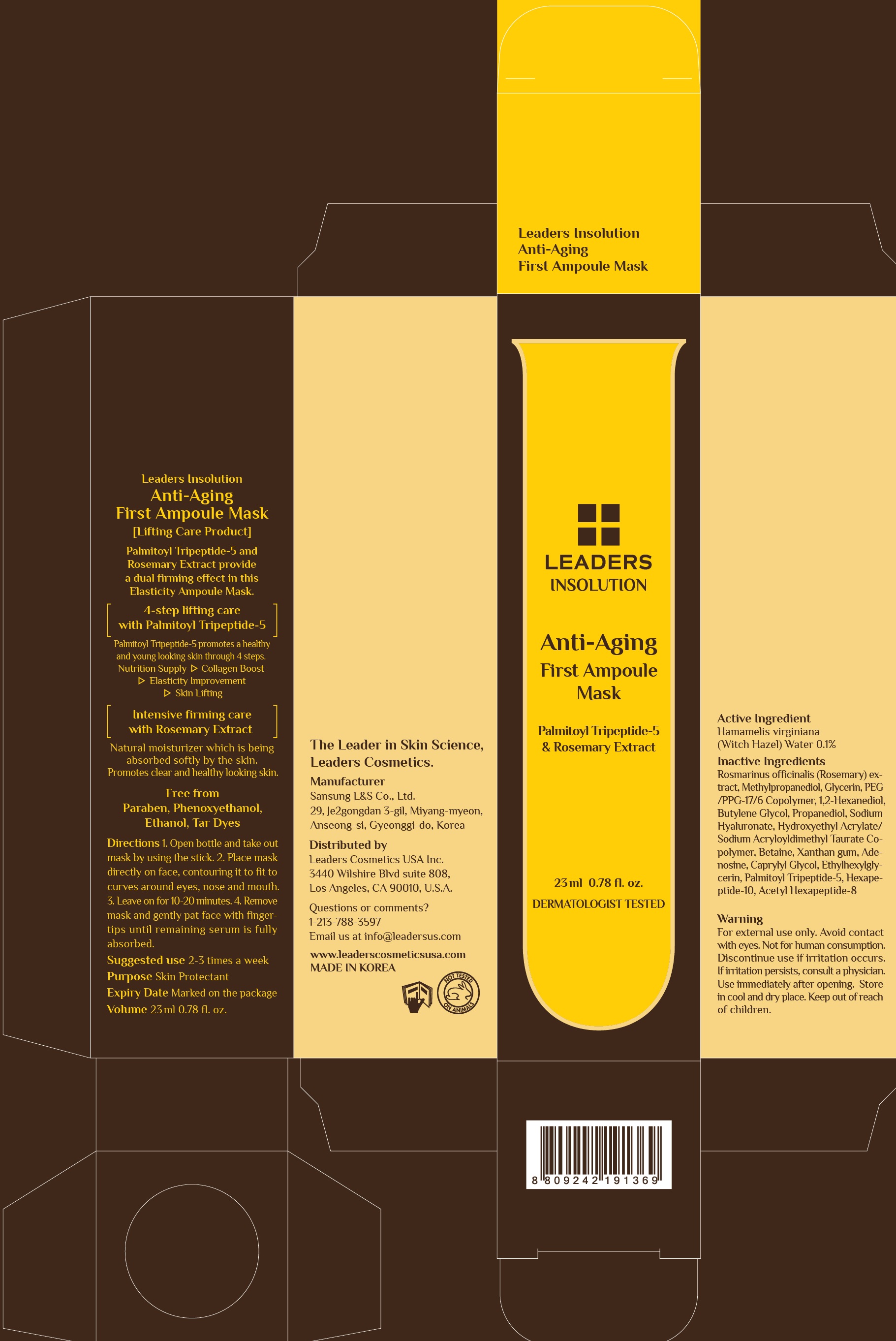 DRUG LABEL: Leaders Anti Aging First Ampoule Mask
NDC: 69424-550 | Form: PATCH
Manufacturer: SANSUNG LIFE & SCIENCE CO., LTD.
Category: otc | Type: HUMAN OTC DRUG LABEL
Date: 20160217

ACTIVE INGREDIENTS: Witch Hazel 23 mg/23 mL
INACTIVE INGREDIENTS: ROSMARINUS OFFICINALIS FLOWERING TOP; Methylpropanediol

ACTIVE INGREDIENT

Active Ingredient: Hamamelis virginiana (Witch Hazel) Water 0.1%

INACTIVE INGREDIENT

Inactive Ingredients: Rosmarinus Officinalis (Rosemary) Extract, Methylpropanediol, Glycerin, PEG/PPG-17/6 Copolymer, 1,2-Hexanediol, Butylene Glycol, Propanediol, Sodium Hyaluronate, Hydroxyethyl Acrylate/Sodium Acryloyldimethyl Taurate Copolymer, Betaine, Xanthan Gum, Adenosine, Caprylyl Glycol, Ethylhexylglycerin, Palmitoyl Tripeptide-5, Hexapeptide-10, Acetyl Hexapeptide-8

PURPOSE

Purpose: Skin Protectant

WARNINGS

Warnings: For external use only. Avoid contact with eyes. Not for human consumption. Discontinue use if irritation occurs. If irritation persists, consult a physician. Use immediately after opening. Store in cool and dry place. Keep out of reach of children.

KEEP OUT OF REACH OF CHILDREN

Directions

Directions: 1. Open bottle and take out mask by using the stick. 2. Place mask directly on face, contouring it to fit to curves around eyes, nose and mouth. 3. Leave on for 10-20 minutes. 4. Remove mask and gently pat face with fingertips until remaining serum is fully absorbed.

Suggested use 2-3 times a week

Directions

Directions: 1. Open bottle and take out mask by using the stick. 2. Place mask directly on face, contouring it to fit to curves around eyes, nose and mouth. 3. Leave on for 10-20 minutes. 4. Remove mask and gently pat face with fingertips until remaining serum is fully absorbed.

Suggested use 2-3 times a week